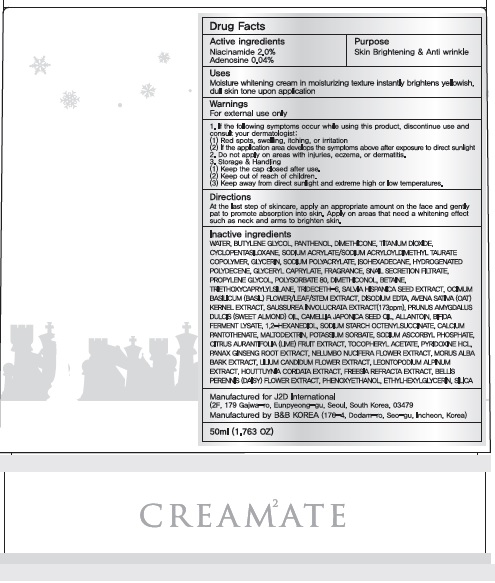 DRUG LABEL: CRE AM2ATE Queen Snow Lotus
NDC: 69958-120 | Form: CREAM
Manufacturer: J2D INTERNATIONAL
Category: otc | Type: HUMAN OTC DRUG LABEL
Date: 20170927

ACTIVE INGREDIENTS: Niacinamide 1.0 g/50 mL; Adenosine 0.02 g/50 mL
INACTIVE INGREDIENTS: WATER; BUTYLENE GLYCOL

ACTIVE INGREDIENT

Active ingredients: Niacinamide 2.0%, Adenosine 0.04%

INACTIVE INGREDIENT

Inactive ingredients: WATER, BUTYLENE GLYCOL, PANTHENOL , DIMETHICONE, TITANIUM DIOXIDE, CYCLOPENTASILOXANE, SODIUM ACRYLATE/SODIUM ACRYLOYLDIMETHYL TAURATE COPOLYMER, GLYCERIN, SODIUM POLYACRYLATE, ISOHEXADECANE, HYDROGENATED POLYDECENE, GLYCERYL CAPRYLATE, FRAGRANCE, SNAIL SECRETION FILTRATE, PROPYLENE GLYCOL, POLYSORBATE 80, DIMETHICONOL, BETAINE, TRIETHOXYCAPRYLYLSILANE, TRIDECETH-6, SALVIA HISPANICA SEED EXTRACT, OCIMUM BASILICUM (BASIL) FLOWER/LEAF/STEM EXTRACT, DISODIUM EDTA, AVENA SATIVA (OAT) KERNEL EXTRACT, SAUSSUREA INVOLUCRATA EXTRACT(173ppm), PRUNUS AMYGDALUS DULCIS (SWEET ALMOND) OIL, CAMELLIA JAPONICA SEED OIL, ALLANTOIN, BIFIDA FERMENT LYSATE, 1,2-HEXANEDIOL, SODIUM STARCH OCTENYLSUCCINATE, CALCIUM PANTOTHENATE, MALTODEXTRIN, POTASSIUM SORBATE, SODIUM ASCORBYL PHOSPHATE, CITRUS AURANTIFOLIA (LIME) FRUIT EXTRACT, TOCOPHERYL ACETATE, PYRIDOXINE HCL, PANAX GINSENG ROOT EXTRACT, NELUMBO NUCIFERA FLOWER EXTRACT, MORUS ALBA BARK EXTRACT, LILIUM CANDIDUM FLOWER EXTRACT, LEONTOPODIUM ALPINUM EXTRACT, HOUTTUYNIA CORDATA EXTRACT, FREESIA REFRACTA EXTRACT, BELLIS PERENNIS (DAISY) FLOWER EXTRACT, PHENOXYETHANOL, ETHYLHEXYLGLYCERIN, SILICA

PURPOSE

Purpose: Skin Brightening & Anti wrinkle

WARNINGS

Warnings: For external use only

1. If the following symptoms occur while using this product, discontinue use and consult your dermatologist: (1) Red spots, swelling, itching, or irritation (2) If the application area develops the symptoms above after exposure to direct sunlight

2. Do not apply on areas with injuries, eczema, or dermatitis.

3. Storage & Handling (1) Keep the cap closed after use. (2) Keep out of reach of children. (3) Keep away from direct sunlight and extreme high or low temperatures.

KEEP OUT OF REACH OF CHILDREN

Uses

Uses: Moisture whitening cream in moisturizing texture instantly brightens yellowish, dull skin tone upon application

Directions

Directions: At the last step of skincare, apply an appropriate amount on the face and gently pat to promote absorption into skin. Apply on areas that need a whitening effect such as neck and arms to brighten skin.